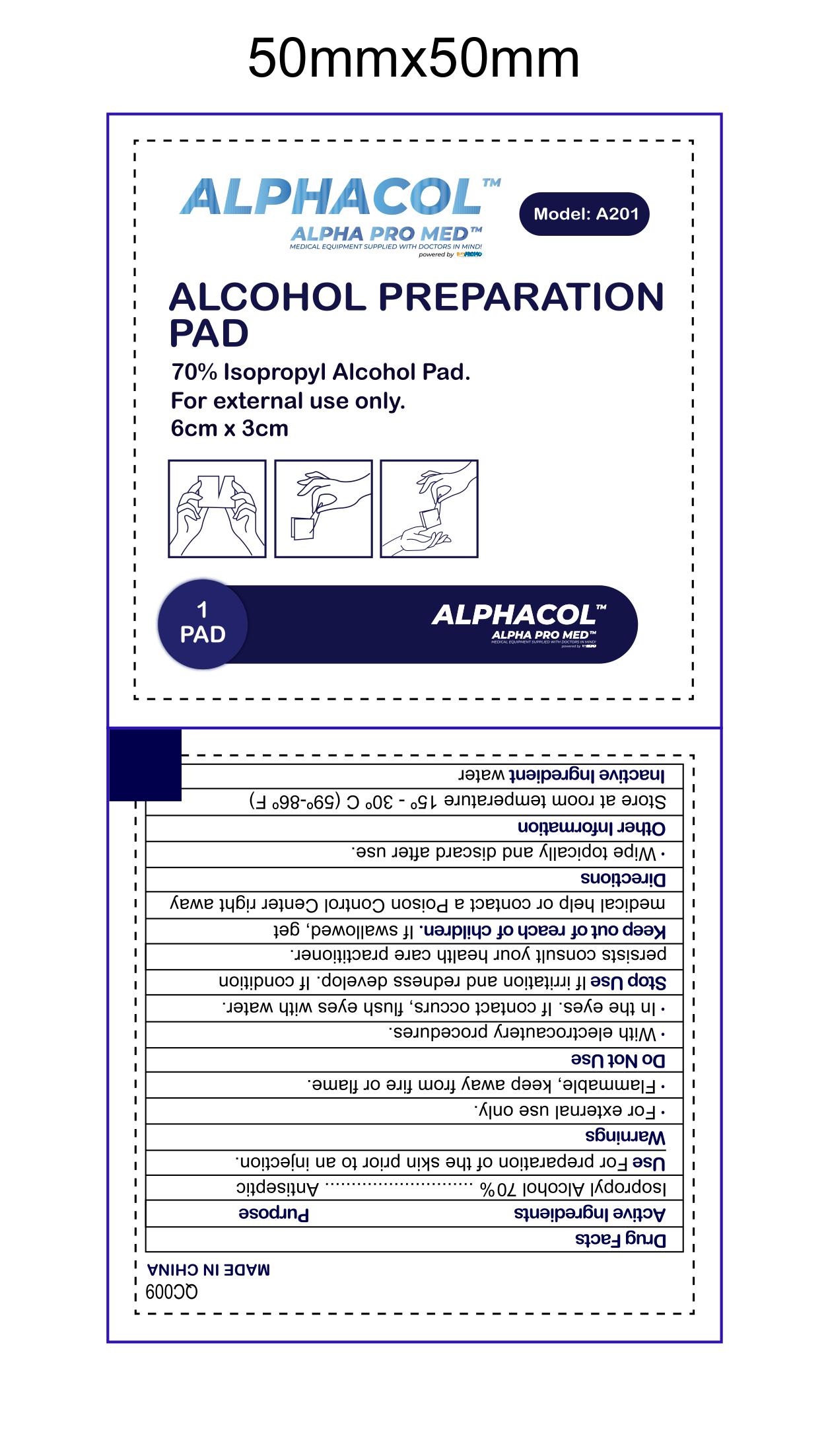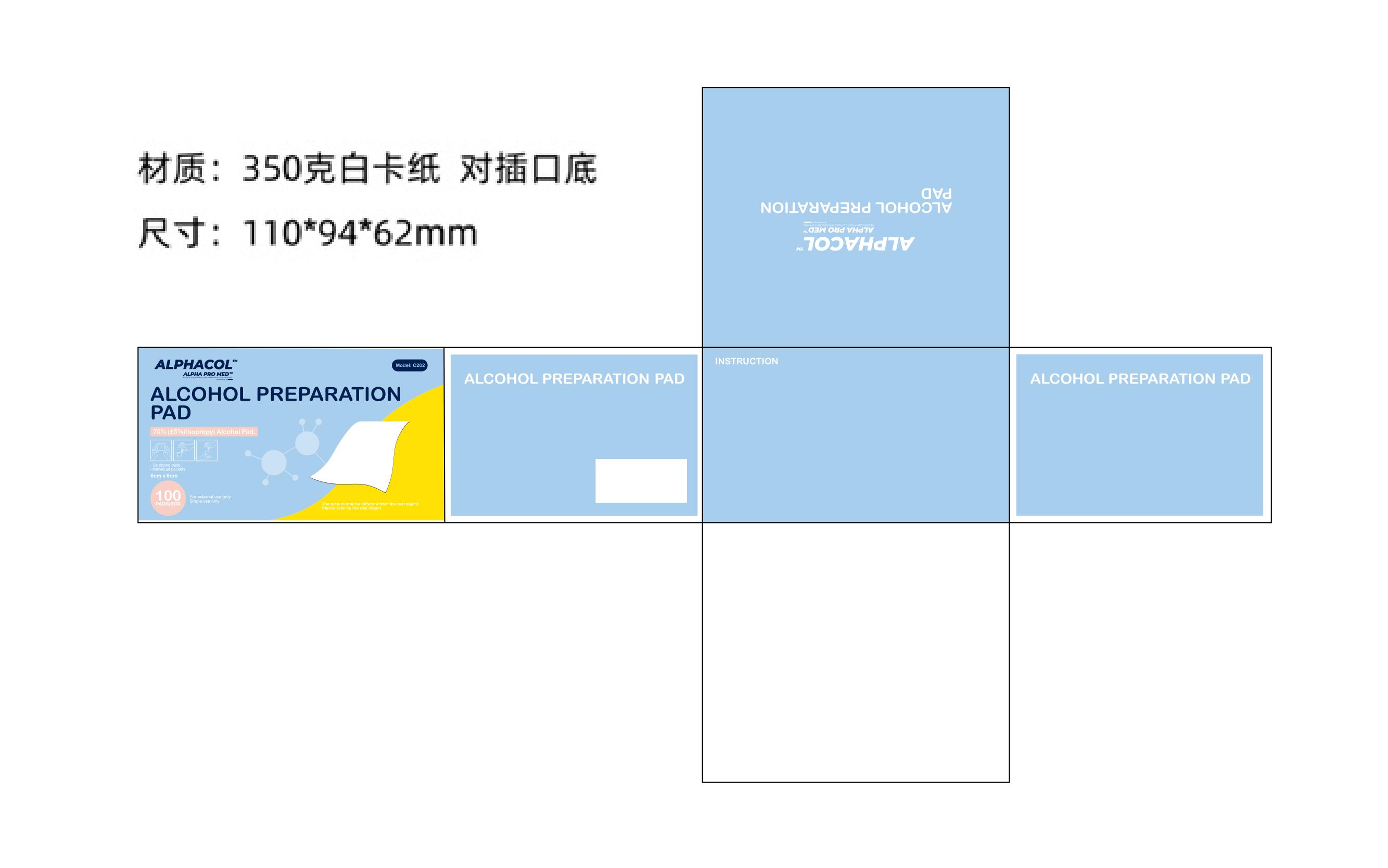 DRUG LABEL: AlphaProMed AlphaCol Sterile Isopropyl Alcohol Preparation Pad
NDC: 81444-002 | Form: CLOTH
Manufacturer: Bay Promo, LLC
Category: otc | Type: HUMAN OTC DRUG LABEL
Date: 20210215

ACTIVE INGREDIENTS: ISOPROPYL ALCOHOL 70 mL/100 mL
INACTIVE INGREDIENTS: WATER

AlphaProMed AlphaCol Sterile Isopropyl Alcohol Preparation Pad

ACTIVE INGREDIENT

Isopropyl Alcohol 70%......................Antiseptic

PURPOSE

Antiseptic

Use

For preparation of the skin prior to an injection

Warnings

- For external use only.
- Flammable, keep away from fire or flame.

Do not use

- with electrocautery procedures.
- in the eyes. If contact occurs, flush eyes with water.

Stop use

if irritation and redness develop.If condition persists consult your health care parctitioner.

Keep out of reach of children. If swallowed, get medical help or contact a Poison Control Center right away

Directions

Wipe topically and discard after use.

Other information

Store at room temperature 15-30C (59-86F)

INACTIVE INGREDIENT

Water